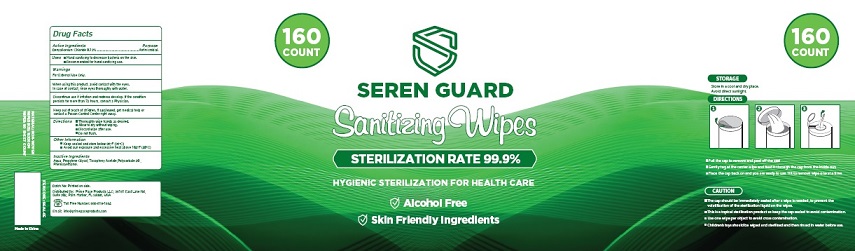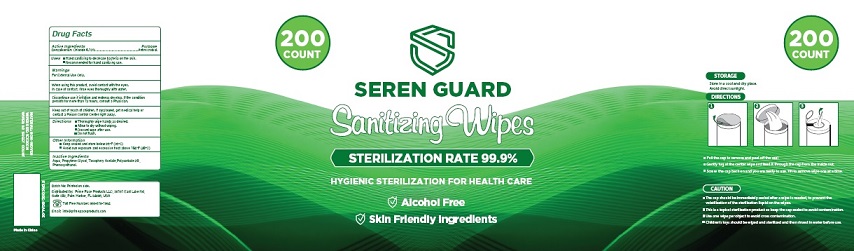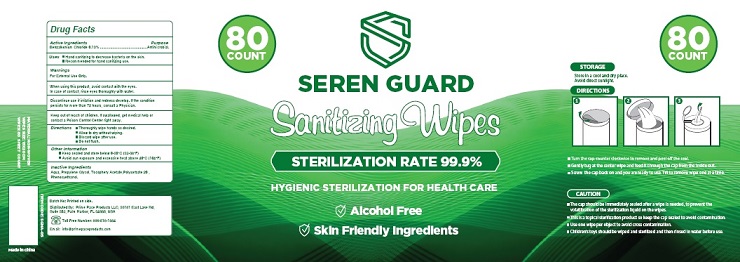 DRUG LABEL: SEREN GUARD Sanitizing Wipes
NDC: 79183-401 | Form: PATCH
Manufacturer: Prime Pace Products LLC
Category: otc | Type: HUMAN OTC DRUG LABEL
Date: 20201206

ACTIVE INGREDIENTS: BENZALKONIUM CHLORIDE 0.13 g/100 g
INACTIVE INGREDIENTS: WATER; PROPYLENE GLYCOL; .ALPHA.-TOCOPHEROL ACETATE; POLYSORBATE 20; PHENOXYETHANOL

SEREN GUARD Sanitizing Wipes

Drug Facts

Active Ingredients

Benzalkonium Chloride 0.13%

Purpose

Antimicrobial

Uses

■ Hand sanitizing to decrease bacteria on the skin.
■ Recommended for hand sanitizing use.

Warnings

For external use only.

When using this product, avoid contact with the eyes.
In case of contact, rinse eyes thoroughly with water.

STOP USE

Discontinue use if irritation and redness develop. If the condition
persists for more than 72 hours, consult a Physician.

Keep out of reach of children. If swallowed, get medical help or contact a Poison Control Center right away.

Directions

■ Thoroughly wipe hands as desired.
■ Allow to dry without wiping.
■ Discard wipe after use.
■ Do not flush.

Other Information

■ Keep sealed and store below 0-30°C (32-38°F)
■ Avoid sun exposure and excessive heat above 40°C (104°F)

Inactive Ingredients

Aqua, Propylene Glycol, Tocophery Acetate,Polysorbate 20 ,
Phenoxyethanol.

Package Label - Principal Display Panel

80
COUNT

SEREN GUARD

Sanitizig Wipes

STERILIZATION RATE 99.9%

HYGIENIC STERILIZATION FOR HEALTH CARE

Alcohol Free

Skin Friendly Ingredients
Alcohol Free

STORAGE
Store in a cool and dry place.
Avoid direct sunlight.

DIRECTIONS
■Turn the cap counter clockwise to remove and peel off the seal.
■ Gently tug at the center wipe and feed it through the cap from the inside out.
■ Screw the cap back on and you are ready to use. Tilt to remove wipe one at a time.

Skin friendly ingredients.

ITEM CODE : SGNA-05

MATERIAL: NON-WOVEN
WIPES SIZE: 15X20CM
WIPES: 80 SHEET COUNT

Batch No: Printed on side.
Distributed By: Prime Pace Products LLC, 36181 East Lake Rd,
Suite 302, Palm Harbor, FL 34685, USA
Toll Free Number: 866-518-1984
Email: info@primepaceproducts.com

Made in China

80 Count

160 Count

200 Count

res